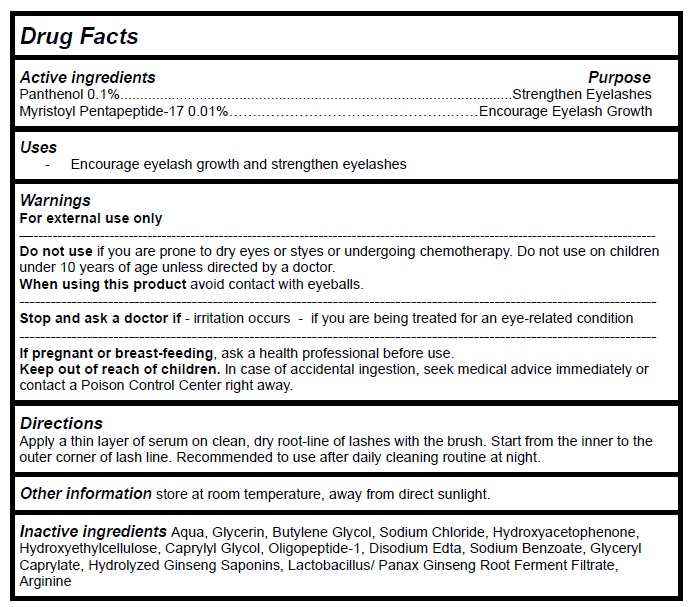 DRUG LABEL: Eyelash Growth Serum
NDC: 83497-001 | Form: LIQUID
Manufacturer: Guangzhou Homar Bio Technology Co. Ltd
Category: otc | Type: HUMAN OTC DRUG LABEL
Date: 20230727

ACTIVE INGREDIENTS: PANTHENOL 0.1 g/100 mL; MYRISTOYL PENTAPEPTIDE-4 0.01 g/100 mL
INACTIVE INGREDIENTS: WATER; GLYCERIN; BUTYLENE GLYCOL; SODIUM CHLORIDE; HYDROXYACETOPHENONE; HYDROXYETHYL CELLULOSE, UNSPECIFIED; CAPRYLYL GLYCOL; OLIGOPEPTIDE-10; EDETATE DISODIUM ANHYDROUS; SODIUM BENZOATE; GLYCERYL MONOCAPRYLATE; GINSENOSIDES; ASIAN GINSENG; ARGININE

Active Ingredient Purpose

Panthenol 0.1%............................................Strengthen Eyelashes
Myristoyl Pentapeptide-17 0.01%…….………….……Encourage Eyelash Growth

Uses

Encourage eyelash growth and strengthen eyelashes

Warnings

For external use only.

Do not use ifyou are prone to dry eyes or styes or undergoing chemotherapy. Do not use on children

under 10 years of age unless directed by a doctor.

When using this productavoid contact with eyeballs.

Stop and ask a doctor if- irritation occurs - if you are being treated for an eye-related condition

If pregnant or breast-feeding, ask a health professional before use.

Keep out of reach of children. In case of accidental ingestion, seek medical advice immediately or contact a Poison Control Center right away.

Directions

Apply a thin layer of serum on clean, dry root-line of lashes with the brush. Start from the inner to the outer corner of lash line. Recommended to use after daily cleaning routine at night.

Other information

store at room temperature, away from direct sunlight.

Inactive ingredients

Aqua, Glycerin, Butylene Glycol, Sodium Chloride, Hydroxyacetophenone, Hydroxyethylcellulose, Caprylyl Glycol, Oligopeptide-1, Disodium Edta, Sodium Benzoate, Glyceryl Caprylate, Hydrolyzed Ginseng Saponins, Lactobacillus/ Panax Ginseng Root Ferment Filtrate, Arginine